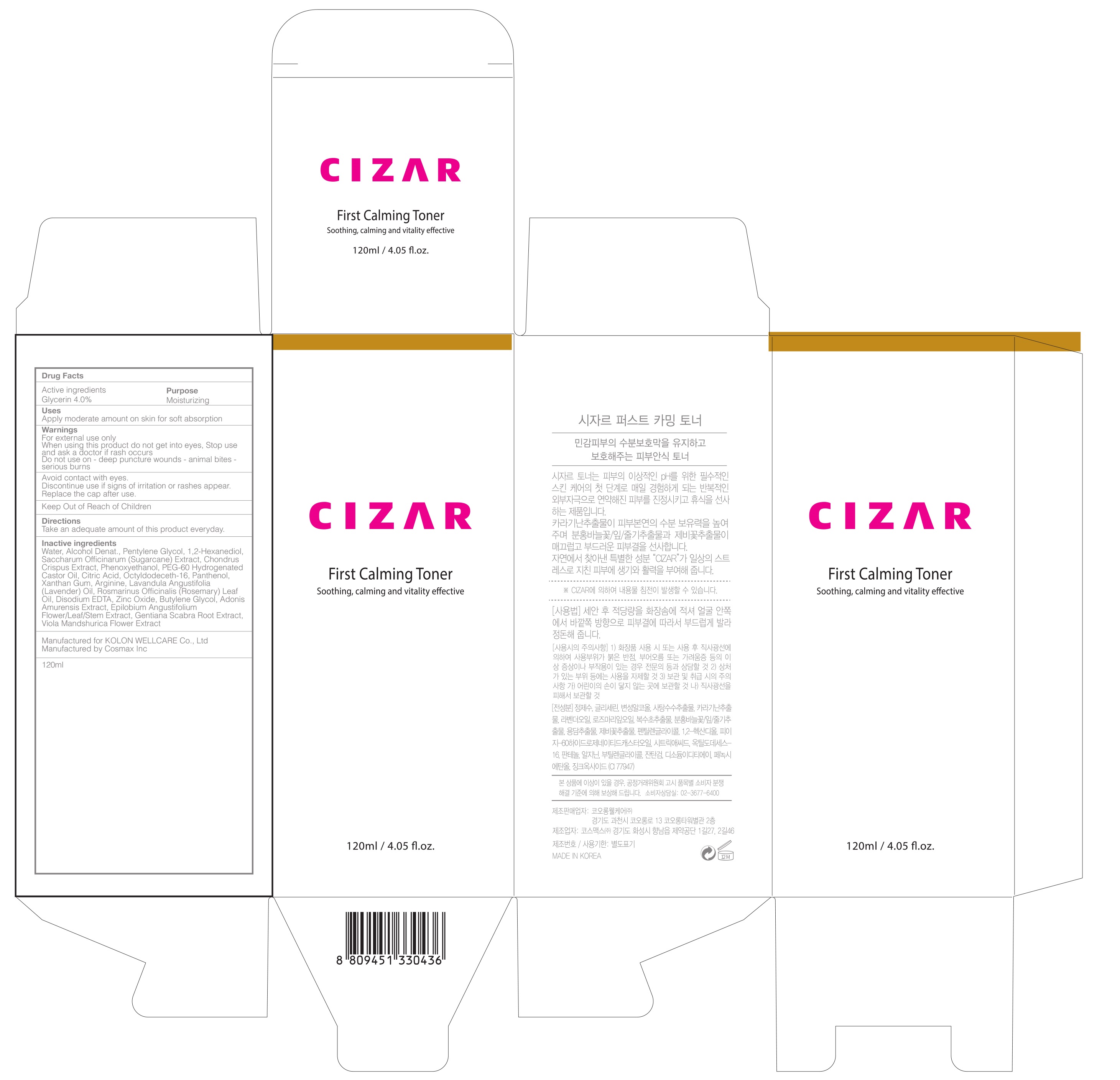 DRUG LABEL: CIZAR First Calming Toner
NDC: 71128-040 | Form: LIQUID
Manufacturer: Tissuegene,inc
Category: otc | Type: HUMAN OTC DRUG LABEL
Date: 20181217

ACTIVE INGREDIENTS: Glycerin 4.8 g/120 mL
INACTIVE INGREDIENTS: Water; Pentylene Glycol

ACTIVE INGREDIENT

Active ingredients: Glycerin 4.0%

INACTIVE INGREDIENT

Inactive ingredients: Water, Alcohol Denat., Pentylene Glycol, 1,2-Hexanediol, Saccharum Officinarum (Sugarcane) Extract, Chondrus Crispus Extract, Phenoxyethanol, PEG-60 Hydrogenated Castor Oil, Citric Acid, Octyldodeceth-16, Panthenol, Xanthan Gum, Arginine, Lavandula Angustifolia (Lavender) Oil, Rosmarinus Officinalis (Rosemary) Leaf Oil, Disodium EDTA, Zinc Oxide, Butylene Glycol, Adonis Amurensis Extract, Epilobium Angustifolium Flower/Leaf/Stem Extract, Gentiana Scabra Root Extract, Viola Mandshurica Flower Extract

PURPOSE

Purpose: Moisturizing

WARNINGS

For external use only When using this product do not get into eyes, Stop use and ask a doctor if rash occurs Do not use on - deep puncture wounds - animal bites - serious burns

Avoid contact with eyes. Discontinue use if signs of irritation or rashes appear. Replace the cap after use. Keep Out of Reach of Children

KEEP OUT OF REACH OF CHILDREN

Uses

Uses: Apply moderate amount on skin for soft absorption

Directions

Directions: Take an adequate amount of this product everyday.